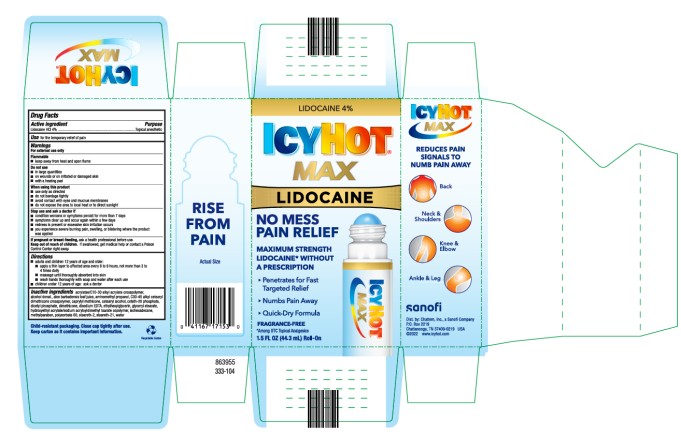 DRUG LABEL: Icy Hot Lidocaine No-Mess
NDC: 41167-1711 | Form: LIQUID
Manufacturer: Chattem, Inc.
Category: otc | Type: HUMAN OTC DRUG LABEL
Date: 20230901

ACTIVE INGREDIENTS: LIDOCAINE HYDROCHLORIDE 4 g/100 g
INACTIVE INGREDIENTS: ACRYLATES/C10-30 ALKYL ACRYLATE CROSSPOLYMER (60000 MPA.S); ALCOHOL; ALOE VERA LEAF; AMINOMETHYLPROPANOL; C30-45 ALKYL CETEARYL DIMETHICONE CROSSPOLYMER; CAPRYLYL METHICONE; CETEARYL ALCOHOL; CETETH-20 PHOSPHATE; DICETYL PHOSPHATE; DIMETHICONE; EDETATE DISODIUM; ETHYLHEXYLGLYCERIN; GLYCERYL STEARATE; HYDROXYETHYL ACRYLATE/SODIUM ACRYLOYLDIMETHYL TAURATE COPOLYMER (100000 MPA.S AT 1.5%); ISOHEXADECANE; METHYLPARABEN; POLYSORBATE 60; STEARETH-2; STEARETH-21; WATER

Icy Hot Max Lidocaine No Mess

ICY HOT with LIDOCAINE CREAM (MAX)

Drug Facts

Active ingredient

Lidocaine HCl 4%

Purpose

Topical anesthetic

Use

for the temporary relief of pain

Warnings

For external use only

Flammable

■ keep away from heat and open flame.

Do not use

■ in large quantities

■ on wounds or on irritated or damaged skin

■ with a heating pad

When using this product

■ use only as directed

■ do not bandage tightly

■ avoid contact with eyes and mucous membranes

■ do not expose the area to local heat or to direct sunlight

Stop use and ask a doctor if

■ condition worsens or symptoms persist for more than 7 days

■ symptoms clear up and occur again within a few days

■ redness is present or excessive skin irritation occurs

■ you experience severe burning pain, swelling, or blistering where the product was applied

Keep out of reach of children.

If swallowed, get medical help or contact a Poison Control Center right away.

Directions

■ adults and children 12 years of age and older:

■ apply a thin layer to affected area every 6 to 8 hours, not more than 3 to 4 times daily

■ massage until thoroughly absorbed into skin

■ wash hands thoroughly with soap and water after each use

■ children under 12 years of age: ask a doctor

Inactive ingredients

acrylates/C10-30 alkyl acrylate crosspolymer, alcohol denat. (15%), aloe barbadensis leaf juice, aminomethyl propanol, C30-45 alkyl cetearyl dimethicone crosspolymer, caprylyl methicone, cetearyl alcohol, ceteth-20 phosphate, dicetyl phosphate, dimethicone, disodium EDTA, ethylhexylglycerin, glyceryl stearate, hydroxyethyl acrylate/sodium acryloyldimethyl taurate copolymer, isohexadecane, methylparaben, polysorbate 60, steareth-2, steareth-21, water

Child-resistant packaging. Close cap tightly after use.

Keep carton as it contains important information.

PRINCIPAL DISPLAY PANEL

Lidocaine 4%
IcyHot
Max